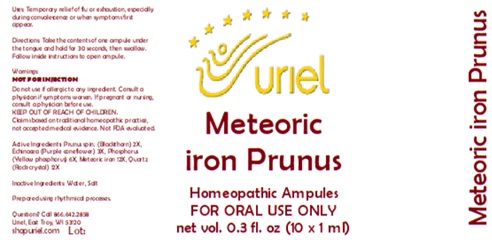 DRUG LABEL: Meteoric Iron Prunus
NDC: 48951-7052 | Form: LIQUID
Manufacturer: Uriel Pharmacy Inc.
Category: homeopathic | Type: HUMAN OTC DRUG LABEL
Date: 20260203

ACTIVE INGREDIENTS: SLOE 2 [hp_X]/1 mL; ECHINACEA, UNSPECIFIED 3 [hp_X]/1 mL; PHOSPHORUS 6 [hp_X]/1 mL; IRON 12 [hp_X]/1 mL; SILICON DIOXIDE 12 [hp_X]/1 mL
INACTIVE INGREDIENTS: SODIUM CHLORIDE; WATER

Meteoric Iron Prunus

PURPOSE

Uses: Temporary relief of flu o rexhaustion, especially during convalescence or when symptoms first appear.

INDICATIONS AND USAGE

FOR ORAL USE ONLY

DOSAGE AND ADMINISTRATION

Directions: Take the contents of one ampule under the tongue and hold for 30 seconds, then swallow. Follow inside instructions to open ampule.

Warnings:
NOT FOR INJECTION
Do not use if allergic to any ingredient. Consult a physician if symptoms worsen. If pregnant or nursing, consult a physician before use.
Claims based on traditional homeopathic practice, not accepted medical evidence. Not FDA evaluated.

KEEP OUT OF REACH OF CHILDREN.

ACTIVE INGREDIENT

Active Ingredients: Prunus spin. (Blackthorn) 2X, Echinacea (Purple coneflower) 3X, Phosphorus (Yellow phosphorus) 6X, Meteoric iron 12X, Quartz (Rock crystal) 12X

Inactive Ingredients: Water, Salt

Prepared using rhythmical processes.

Questions? Call 866.642.2858
Uriel, East Troy, WI 53120
shopuriel.com

Lot: